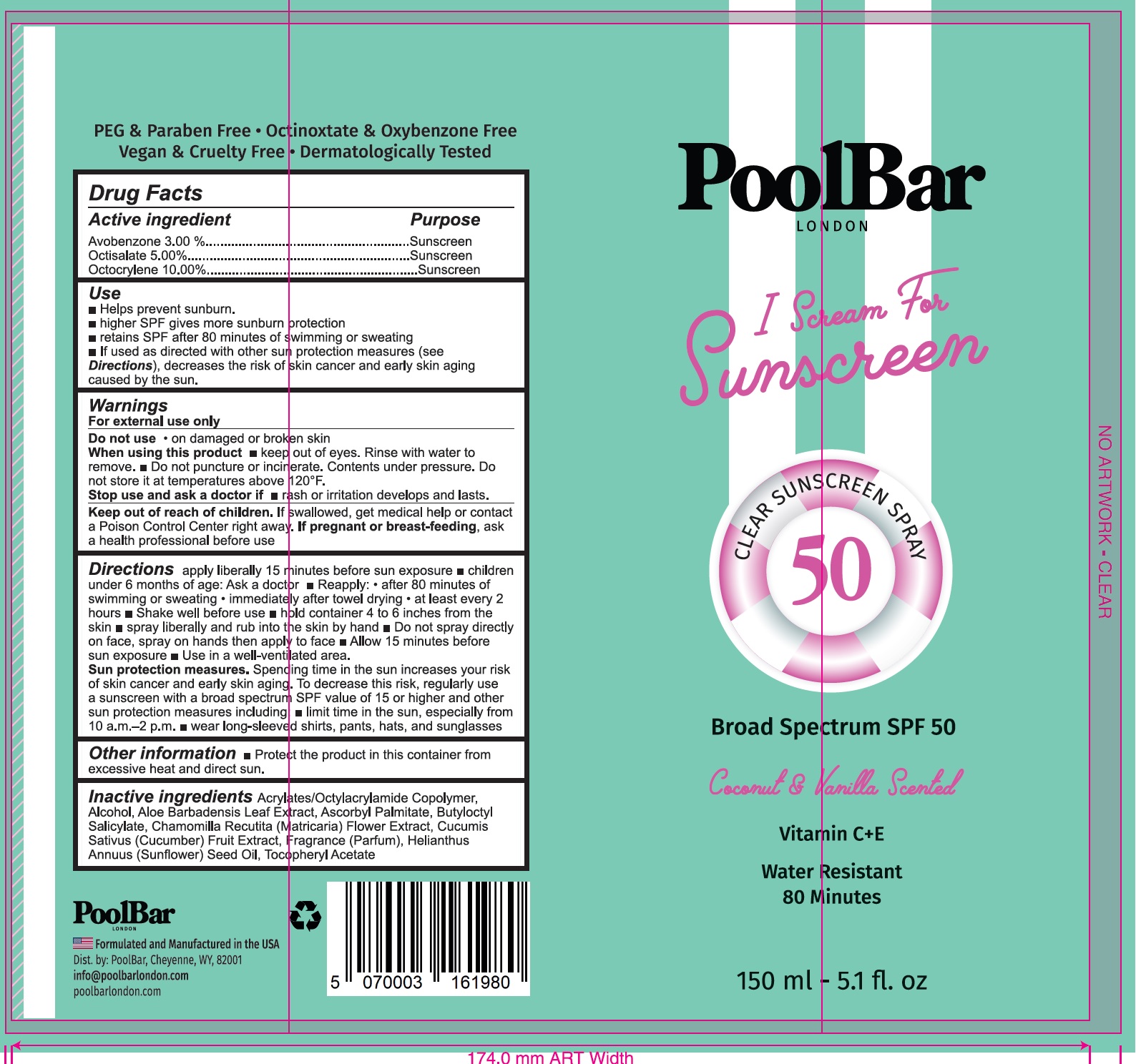 DRUG LABEL: PoolBar I Scream For Sunscreen SPF 50 Coconut and Vanilla
NDC: 84953-874 | Form: LIQUID
Manufacturer: POOLBAR
Category: otc | Type: HUMAN OTC DRUG LABEL
Date: 20250806

ACTIVE INGREDIENTS: AVOBENZONE 30 mg/1 mL; OCTISALATE 50 mg/1 mL; OCTOCRYLENE 100 mg/1 mL
INACTIVE INGREDIENTS: ALCOHOL; ALOE VERA LEAF; ASCORBYL PALMITATE; BUTYLOCTYL SALICYLATE; CHAMOMILE; CUCUMBER; COCONUT OIL; SUNFLOWER OIL; .ALPHA.-TOCOPHEROL ACETATE

PoolBar I Scream For Sunscreen SPF 50, Coconut & Vanilla

Active ingredient

Avobenzone 3.00%
Octisalate 5.00%
Octocrylene 10.00%

Purpose

Sunscreen

Use

- Helps prevent sunburn.
- higher SPF gives more sunburn protection
- retains SPF after 80 minutes of swimming or sweating
- If used as directed with other sun protection measures (see Directions), decreases the risk of skin cancer and early skin aging caused by the sun.

Warnings

For external use only

Do not use

- on damaged or broken skin

When using this product

- keep out of eyes. Rinse with water to remove.
- Do not puncture or incinerate. Contents under pressure. Do not store it at temperatures above 120ºF.

Stop use and ask a doctor if

- rash or irritation develops and lasts.

Keep out of reach of children.

If swallowed, get medical help or contact a Poison Control Center right away.

If pregnant or breast-feeding,

ask a health professional before use

Directions

apply liberally 15 minutes before sun exposure

- children under 6 months of age: Ask a doctor.
- Reapply:
- after 80 minutes of swimming or sweating
- immediately after towel drying
- at least every 2 hours
- Shake well before use
- hold container 4 to 6 inches from the skin
- spray liberally and rub into the skin by hand
- Do not spray directly on face. spray into hands and apply to face.
- Allow 15 minutes before sun exposure
- Use in well-ventilated area.
- Sun protection measures.Spending time in the sun increases your risk of skin cancer and early skin aging. To decrease the risk, regularly use a sunscreen with broad spectrum SPF value of 15 or higher and other sun protection measures including:
- limit time in the sun, especially from 10 a.m.-2 p.m.
- wear long-sleeved shirts, pants, hats, and sunglasses

Other information

- Protect the product in this container from excessive heat and direct sun.

Inactive ingredients

Acrylates/Octylacrylamide Copolymer, Alcohol, Aloe Barbadensis Leaf Extract, Ascorbyl Palmitate, Butyloctyl Salicylate, Chamomilla Recutita (Matricaria) Flower Extract, Cucumis Sativus (Cucumber) Fruit Extract, Fragrance (Parfum), Helianthus Annuus (Sunflower) Seed Oil, Tocopheryl Acetate